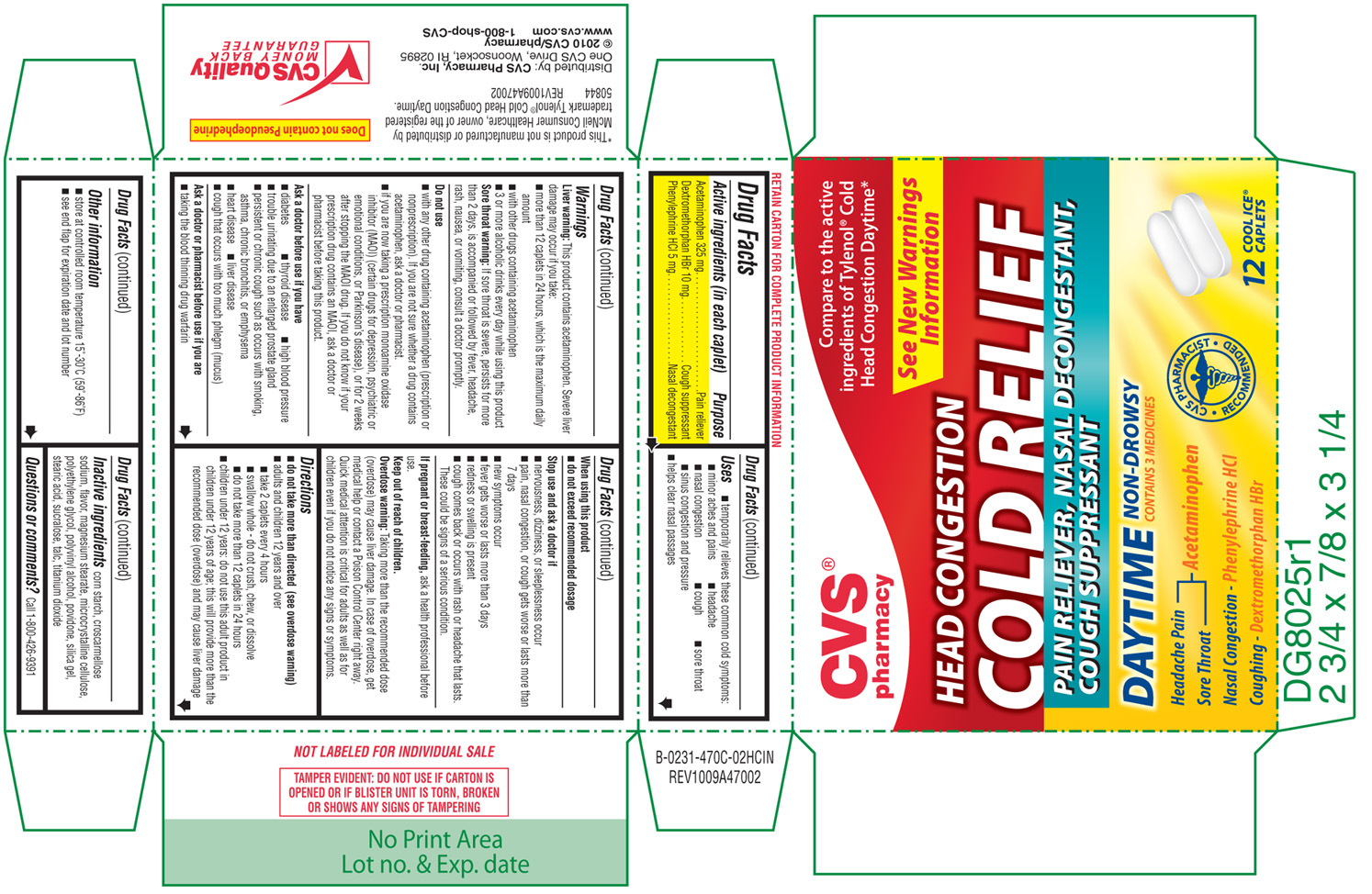 DRUG LABEL: Head Congestion Cold Relief 
NDC: 59779-470 | Form: TABLET, FILM COATED
Manufacturer: WOONSOCKET PRESCRIPTION CENTER, INCORPORATED
Category: otc | Type: HUMAN OTC DRUG LABEL
Date: 20100830

ACTIVE INGREDIENTS: Acetaminophen 325 mg/1 1; Dextromethorphan Hydrobromide 10 mg/1 1; Phenylephrine Hydrochloride 5 mg/1 1
INACTIVE INGREDIENTS: Starch, Corn; Croscarmellose Sodium; Magnesium Stearate; Cellulose, Microcrystalline; Polyethylene Glycol; Polyvinyl Alcohol; Povidone; Silicon Dioxide; Stearic Acid; Sucralose; Talc; Titanium Dioxide

Active ingredients

(in each caplet)

Acetaminophen 325 mg

Dextromethorphan HBr 10 mg

Phenylephrine HCl 5 mg

Purpose

Pain reliever

Cough suppressant

Nasal decongestant

Uses

- temporarily relieves theses common cold symptoms:
- minor aches and pains
- headache
- nasal congestion
- cough
- sore throat
- sinus congestion and pressure
- helps clear nasal passages

Warnings

Liver warning:

This product contains acetaminophen. Severe liver damage may occur if you take:

- more than 12 caplets in 24 hours, which is the maximum daily amount
- with other drugs containing acetaminophen
- 3 or more alcoholic drinks every day while using this product

Sore throat warning:

If sore throat is severe, persists for more than 2 days, is accompanied or followed by fever, headache, rash, nausea, or vommiting, consult a doctor promptly.

Do not use

- with any other drug containing acetaminophen (prescription or nonprescription). If you are not sure whether a drug contains acetaminophen, ask a doctor or pharmacist.
- if you are now taking a prescription monoamine oxidase inhibitor (MAOI) (certain drugs for depression, psychiatric or emotional conditions, or Parkinson's disease), or for 2 weeks after stopping the MAOI drug. If you do not know if your prescription drug contains an MAOI, ask a doctor or pharmacist before taking this product.

Ask a doctor before use if you have

- diabetes
- thyroid disease
- high blood pressure
- trouble urinating due to an enlarged prostate gland
- persistent or chronic cough such as occurs with smoking, asthma, chronic bronchitis, or emphysema
- heart disease
- liver disease
- cough that occurs with too much phlegm (mucus)

Ask a doctor or pharmacist before use if you are

- taking the blood thinning drug warfarin

When using this product

- do not exceed recommended dosage

Stop use and ask a doctor if

- nervousness, dizziness, or sleeplessness occur
- pain, nasal congestion, or cough gets worse or lasts more than 7 days
- new symptoms occur
- fever gets worse or lasts more than 3 days
- redness or swelling is present
- cough comes back or occurs with rash or headache that lasts.

These could be signs of a serious condition.

If pregnant or breast-feeding,

ask a health professional before use.

Keep out of reach of children.

Overdose warning: Taking more than the recommended dose (overdose) may cause liver damage. In case of overdose, get medical help or contact a Poison Control Center right away. Quick medical attention is critical for adults as well as for children even if you do not notice any signs or symptoms.

Directions

- do not take more than directed (see overdose warning)
- adults and children 12 years and over
- take 2 caplets every 4 hours
- swallow whole - do not crush, chew, or dissolve
- do not take more than 12 caplets in 24 hours
- children under 12 years: do not use this adult product in children under 12 years of age; this will provide more than the recommended dose (overdose) and may cause liver damage

Other information

- store at controlled room temperature 15°-30°C (59°-86°F)
- see end flap for expiration date and lot number

Inactive ingredients

corn starch, croscarmellose sodium, flavor, magnesium stearate, microcrystalline cellulose, polyethylene glycol, polyvinyl alcohol, povidone, silica gel, stearic acid, sucralose, talc, titanium dioxide

Questions or comments?

Call 1-800-426-9391

PRODUCT PACKAGING

The product packaging shown below represents a sample of that currently in use. Additional packaging may also be available.

CVS®

pharmacy

Compare to the active

ingredients of Tylenol® Cold

Head Congestion Daytime*

See New Warnings

Information

HEAD CONGESTION

COLD RELIEF

PAIN RELIEVER, NASAL DECONGESTANT,

COUGH SUPPRESSANT

DAYTIME

NON-DROWSY

CONTAINS 3 MEDICINES

Headache Pain -

- Acetaminophen

Sore Throat -

Nasal Congestion - Phenylephrine HCl

Coughing - Dextromethorphan HBr

12 COOL ICE® CAPLETS

TAMPER EVIDENT: DO NOT USE IF CARTON IS OPNENED OR IF BLISTER UNIT IS TORN, BROKEN OR SHOWS ANY SIGNS OF TAMPERING

50844 REV1009A47002

Distributed by: CVS Pharmacy, Inc.

One CVS Drive, Woonsocket, RI 02895

© 2010 CVS/pharmacy

www.cvs.com 1-800-shop-CVS